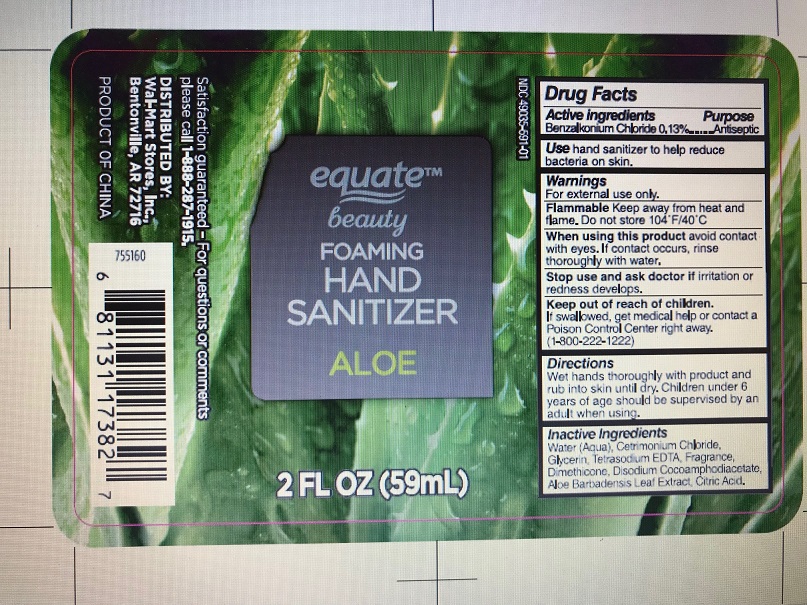 DRUG LABEL: equate
NDC: 49035-591 | Form: LIQUID
Manufacturer: Walmart
Category: otc | Type: HUMAN OTC DRUG LABEL
Date: 20171129

ACTIVE INGREDIENTS: BENZALKONIUM CHLORIDE .13 g/100 mL
INACTIVE INGREDIENTS: WATER; CETRIMONIUM CHLORIDE; GLYCERIN; EDETATE SODIUM; DIMETHICONE; DISODIUM COCOAMPHODIACETATE; ALOE VERA LEAF; CITRIC ACID MONOHYDRATE

DRUG FACTS

Drug Facts

Active Ingredients

Benzalkonium Chloride 0.13%

Inactive Ingredients

Inactive Ingredients: Water (Agua), Cetrimonium Chloride, Glycerine, Tetrasodium EDTA, Fragrance, Dimehicone, Disodium Cocoamphodiacetate, Aloe Barbadensis Leaf Extract, Citric Acid.

Purpose

Antiseptic

Uses AND Directions

Use hand sanitizer to help reduce bacteria on skin.

Directions

Wet hands thoroughly with product and rub into skin until dry. Children under 6 ears of age should be supervised by an adult when using.

Warnings

For external use only.

Flammable Keep away from heat and flame. Do not store 104o F/40o C

Keep out of reach of children. If swallowed get medical help or contact a Poison Control Center right away. (1-800-222-1222)

Keep out of reach of children If swallowed, get medical help or contact a Poison Control Center right away

When using

When using this product avoid contact with eyes. If contact occurs, rinse thoroughly with water.

Stop use

Stop use and ask doctor if irritation or redness develops.

Directions

Wet hands thoroughly with product and rub into skin until dry. Children under 6 years of age should be supervised by an adult when using.

PRINCIPAL DISPLAY PANEL – Bottle Label

equate Beauty NDC 49035-591-01

Foaming Hand Sanitizer

Aloe

2 FL oz. (59mL)

Satisfaction guaranteed - For questions or comments please call 1-888-287-1915

DISTRIBUTED BY: Wal-Mart Stores, Inc.

Bentonville, AR 72716

PRODUCT OF CHINA